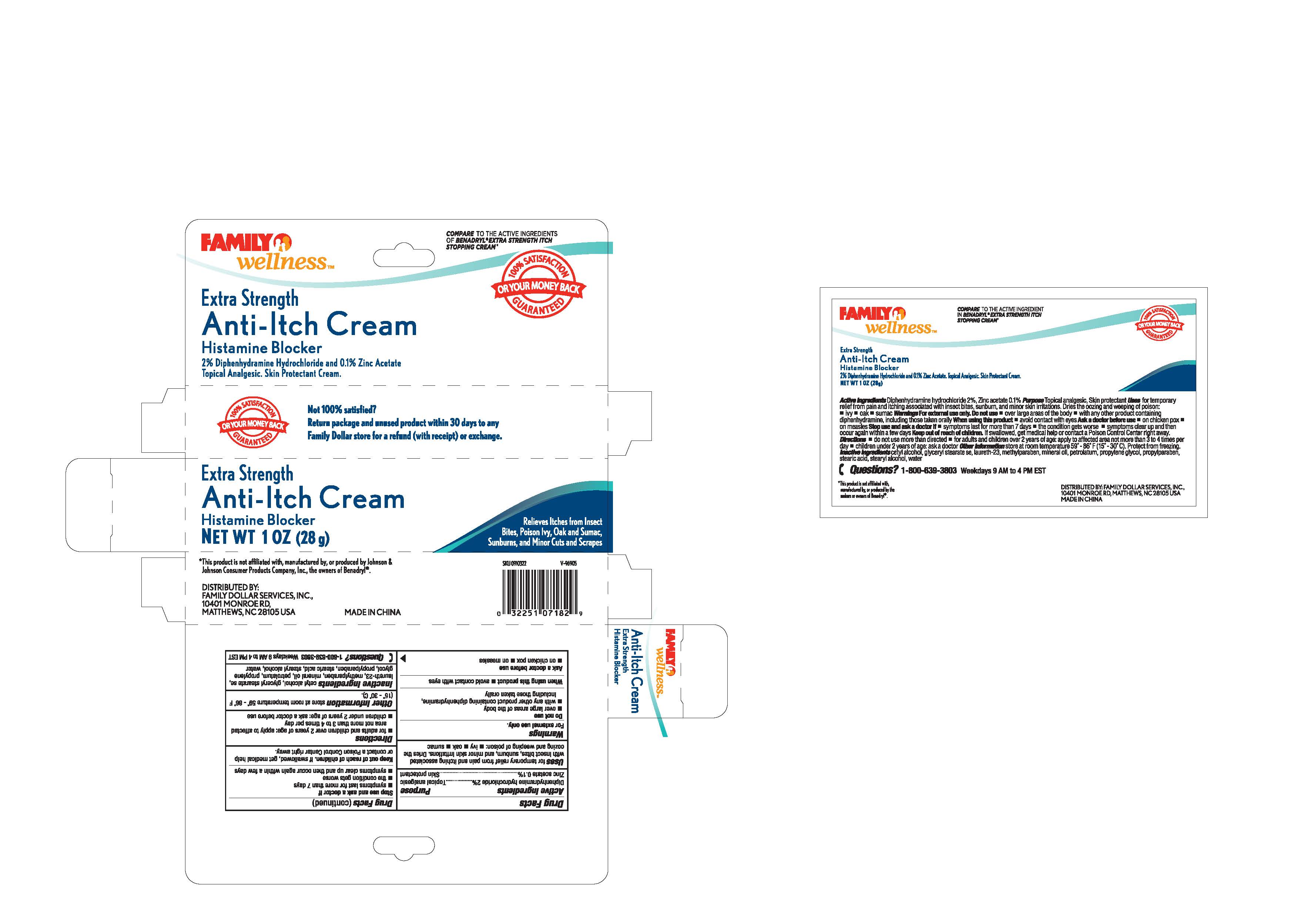 DRUG LABEL: Family Wellness
NDC: 55621-007 | Form: CREAM
Manufacturer: Zhejiang Jingwei Pharmaceutical Co., Ltd.
Category: otc | Type: HUMAN OTC DRUG LABEL
Date: 20231024

ACTIVE INGREDIENTS: DIPHENHYDRAMINE HYDROCHLORIDE 2 g/100 g; ZINC ACETATE 0.1 g/100 g
INACTIVE INGREDIENTS: CETYL ALCOHOL; GLYCERYL MONOSTEARATE; LAURETH-23; METHYLPARABEN; MINERAL OIL; PETROLATUM; PROPYLENE GLYCOL; PROPYLPARABEN; STEARIC ACID; STEARYL ALCOHOL; WATER

Drug Facts

Inactive Ingredients - cetyl alcohol, glycerol stearate,

laureth-23, methylparaben, mineral oil, petrolatum, propylene

glycol, propylparaben, stearic acid, stearyl alcohol, water

Active Ingredients

Diphenhydramine hydrochloride 2 %

Zinc acetate 0.1 %

Purpose

---Topical analgesic

---Skin protectant

INDICATIONS AND USAGE

Uses for temporary relief from pain and itching associated

with insect bites, sunburn and minor skin irritations. Dries the

oozing and weeping of poison: -ivy -oak - sumac

Warnings

For external use only

Do not use

-over large areas of the body

-with any other product containing diphenhydramine,

including those taken orally

When using this product - avoid contact with eyes

Ask a doctor before use

-on chicken pox

-on measles

Stop use and ask a doctor if:

-symptoms last for more than 7 days

-the condition gets worse

-symptoms clear up and then occur again within a few days

Keep out of reach of children. If swallowed, get medical help

or contact a Poison Control Center right away.

Directions

-for adults and children over 2 years of age: apply to affected area

not more than 3 or 4 times per day

-children under 2 years of age: ask a doctor before use

Other information - store at room temperature 59 - 86 F (15 - 30 C)

QUESTIONS

Questions? 1-800-639-3803 Weekdays 9 AM to 4 PM EST